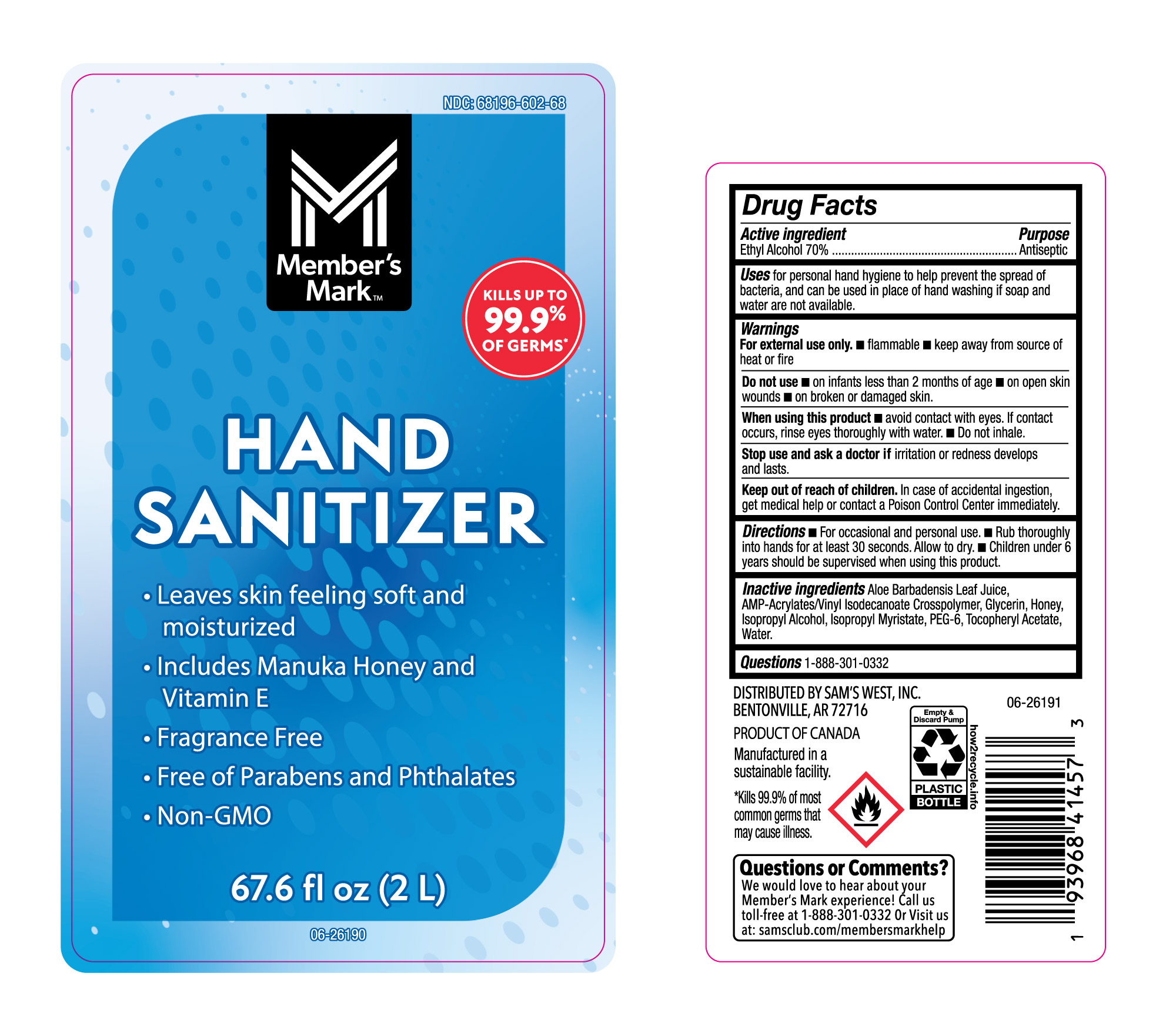 DRUG LABEL: Alcohol
NDC: 68196-602 | Form: LIQUID
Manufacturer: Sam's West Inc
Category: otc | Type: HUMAN OTC DRUG LABEL
Date: 20240723

ACTIVE INGREDIENTS: ALCOHOL 70 mL/100 mL
INACTIVE INGREDIENTS: ACRYLATES/VINYL ISODECANOATE CROSSPOLYMER (10000 MPA.S NEUTRALIZED AT 0.5%); WATER; .ALPHA.-TOCOPHEROL ACETATE; ALOE VERA LEAF; ISOPROPYL ALCOHOL; GLYCERIN; ISOPROPYL MYRISTATE; HONEY; POLYETHYLENE GLYCOL 300

NDC 68196-602-68, Members Mark Hand Sanitizer

Active Ingredient

Ethyl Alcohol 70%

Purpose

Antiseptic

Uses

For personal hand hygiene to help prevent the spread of bacteria, and can be used in place of hand washing if soap and water are not available.

Warnings

For external use only

- Flammable
- Keep away from source of heat or fire.

Do not use

- On infants less than 2 months of age.
- On open skin wounds.
- on broken or damaged skin.

When using this product

- Avoid contact with eyesd. If contact occurs, rinse eyes thoroughly with water.
- Do not Inhale.

Stop use and ask a doctor if

Irritation or redness develops and lasts.

Keep out of reach of children

In case of accidental ingestion, get medical help or contact a Poison Control Center immediately.

Directions

- For occassional and personal use.
- Rub thoroughly into hands for at least 30 seconds. Allow to dry.
- Children under 6 years should be supervised when using this product.

Inactive Ingredients

Aloe Barbadensis Leaf Juice, AMP-Acrylates/Vinyl Isodecanoate Crosspolymer, Glycerin, Honey, Isopropyl Alcohol, Isopropyl Myristate, PEG-6, Tocopheryl Acetate, Water.